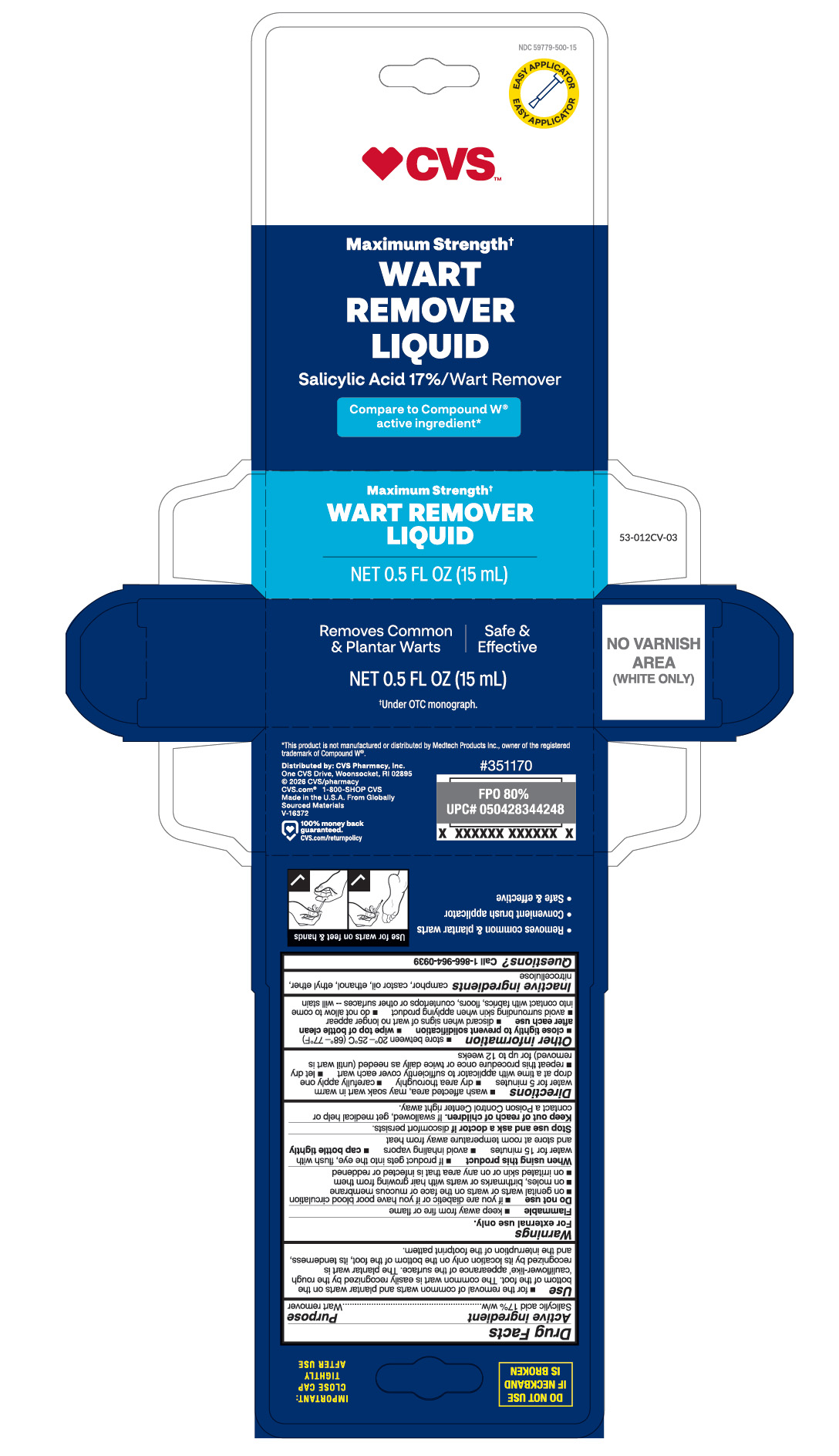 DRUG LABEL: Salicylic Acid
NDC: 59779-500 | Form: LIQUID
Manufacturer: CVS Pharmacy
Category: otc | Type: HUMAN OTC DRUG LABEL
Date: 20260209

ACTIVE INGREDIENTS: SALICYLIC ACID 0.17 mg/15 mL
INACTIVE INGREDIENTS: NITROCELLULOSE; CAMPHOR (NATURAL); CASTOR OIL; ALCOHOL; ETHYL ETHER

CVS Wart Remover Liquid

Active ingredient

Salicylic acid 17%w/w

Purpose

Wart Remover

Use

- for the removal of common warts and plantar warts on the bottom of the foot. The common wart is easily recognized by the rough 'cauliflower-like' appearance of the surface. The plantar wart is recognized by its location only on the bottom of the foot, its tenderness, and the interruption of the footprint pattern.

Warnings

For external use only.

Flammable

- keep away from fire or flame

Do not use

- if you are diabetic or if you have poor blood circulation
- on genital warts or warts on the face or mucous membrane
- on moles, birthmarks or warts with hair growing from them
- on irritated skin or on any area that is infected or reddened

When using this product

- If product gets into the eyes, flush with water for 15 minutes
- avoid inhaling vapors
- cap bottle tightly and store at room temperature away from heat

Stop use and ask doctor if

discomfort persists

Keep out of reach of children.

If swallowed, get medical help or contact a Poison Control Center right away.

Directions

- wash affected area, may soak wart in warm water for 5 minutes
- dry area thoroughly
- carefully apply one drop at a time with applicator to sufficiently cover each wart
- let dry
- repeat this procedure once or twice daily as needed (until wart is removed) for up to 12 weeks

Other information

- store between 20°-25°C (68°-77°F)
- close tightly to prevent solidification
- wipe top of bottle clean after each use
- discard when signs of wart no longer appear
- avoid surrounding skin when applying product
- do not allow to come into contact with fabrics, floors, countertops or other surfaces -- will stain

Inactive ingredients

camphor, castro oil, ethanol, ethyl ether, nitrocellulose

Questions?

Call 1-866-964-0939

RECENT MAJOR CHANGES

..

Principal Display Panel

CVS

Maximum Strength

WART

REMOVER

LIQUID

Salicylic Acid 17%/ Wart Remover

Compare to Compound W

active ingredient

Maximum Strength

WART REMOVER

LIQUID

NET 0.5 FL OZ (15mL)